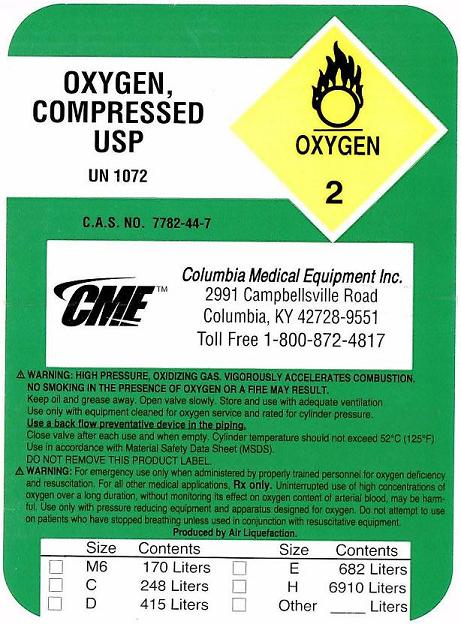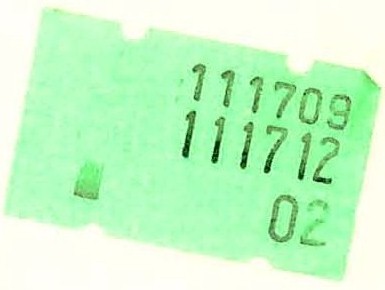 DRUG LABEL: Oxygen
NDC: 65241-0001 | Form: GAS
Manufacturer: Columbia Medical Equipment, Inc.
Category: prescription | Type: HUMAN PRESCRIPTION DRUG LABEL
Date: 20091130

ACTIVE INGREDIENTS: Oxygen 99 L/100 L

Oxygen